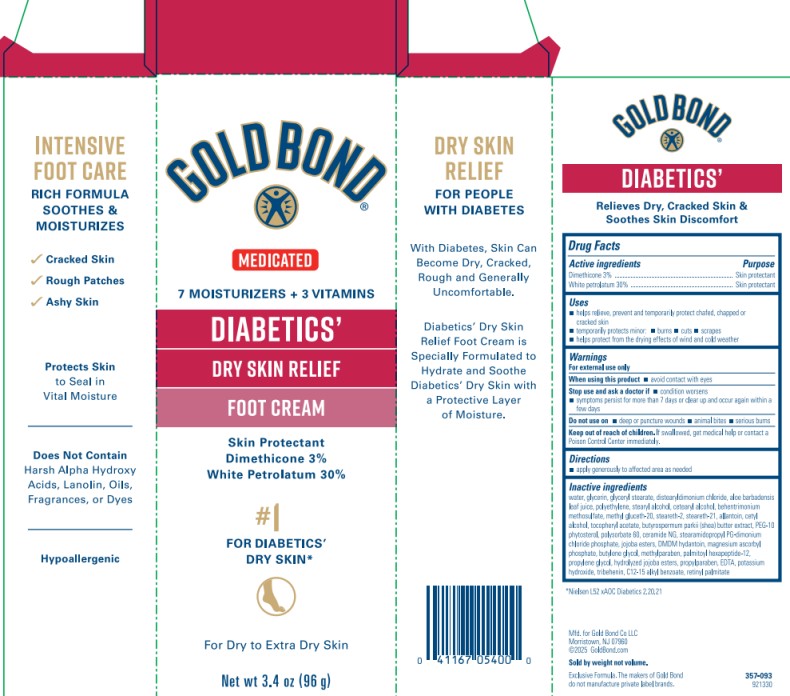 DRUG LABEL: Gold Bond Diabetics Dry Skin Relief Foot Cream
NDC: 84714-0541 | Form: CREAM
Manufacturer: Gold Bond Co LLC
Category: otc | Type: HUMAN OTC DRUG LABEL
Date: 20251204

ACTIVE INGREDIENTS: DIMETHICONE 3 g/100 g; WHITE PETROLATUM 30 g/100 g
INACTIVE INGREDIENTS: WATER; GLYCERIN; GLYCERYL STEARATE; DISTEARYLDIMONIUM CHLORIDE; ALOE BARBADENSIS LEAF JUICE; POLYETHYLENE; STEARYL ALCOHOL; CETEARYL ALCOHOL; BEHENTRIMONIUM METHOSULFATE; METHYL GLUCETH-20; STEARETH-2; STEARETH-21; ALLANTOIN; CETYL ALCOHOL; .ALPHA.-TOCOPHEROL ACETATE; BUTYROSPERMUM PARKII (SHEA) BUTTER; POLYSORBATE 60; CERAMIDE NG; STEARAMIDOPROPYL PG-DIMONIUM CHLORIDE PHOSPHATE; JOJOBA OIL, RANDOMIZED; DMDM HYDANTOIN; MAGNESIUM ASCORBYL PHOSPHATE; BUTYLENE GLYCOL; METHYLPARABEN; PALMITOYL HEXAPEPTIDE-12; PROPYLENE GLYCOL; HYDROLYZED JOJOBA ESTERS; PROPYLPARABEN; EDTA; POTASSIUM HYDROXIDE; TRIBEHENIN; C12-15 ALKYL BENZOATE; RETINYL PALMITATE

Gold Bond Diabetics Dry Skin Relief Foot Cream

Drug Facts – Gold Bond Diabetics’ Dry Skin Relief Foot Cream

Active ingredients

Dimethicone 3%
White petrolatum 30%

Purpose

Skin protectant

Uses

- helps relieve, prevent and temporarily protect chafed, chapped, cracked or windburned skin
- temporarily protects minor burns, cuts, and scrapes
- helps protect from the drying effects of wind and cold weather

Warnings

For external use only

When using this product

- avoid contact with eyes

Stop use and ask a doctor if

- condition worsens
- symptoms persist for more than 7 days or clear up and occur again within a few days

Do not use on

- deep or puncture wounds
- animal bites
- serious burns

Keep out of reach of children.

If swallowed, get medical help or contact a Poison Control Center immediately.

Directions

- apply generously to affected area as needed

Inactive ingredients

water, glycerin, glyceryl stearate, distearyldimonium chloride, aloe barbadensis leaf juice, polyethylene, stearyl alcohol, cetearyl alcohol, behentrimonium methosulfate, methyl gluceth-20, steareth-2, steareth-21, allantoin, cetyl alcohol, tocopheryl acetate, butyrospermum parkii (shea) butter extract, PEG-10 phytosterol, polysorbate 60, ceramide NG, stearamidopropyl PG-dimonium chloride phosphate, jojoba esters, DMDM hydantoin, magnesium ascorbyl phosphate, butylene glycol, methylparaben, palmitoyl hexapeptide-12, propylene glycol, hydrolyzed jojoba esters, propylparaben, EDTA, potassium hydroxide, tribehenin, C12-15 alkyl benzoate, retinyl palmitate

PRINCIPAL DISPLAY PANEL

Gold Bond Skin Protectant Foot Cream
diabetics’
Dry Skin Relief
Net wt 3.4 oz (96 g)